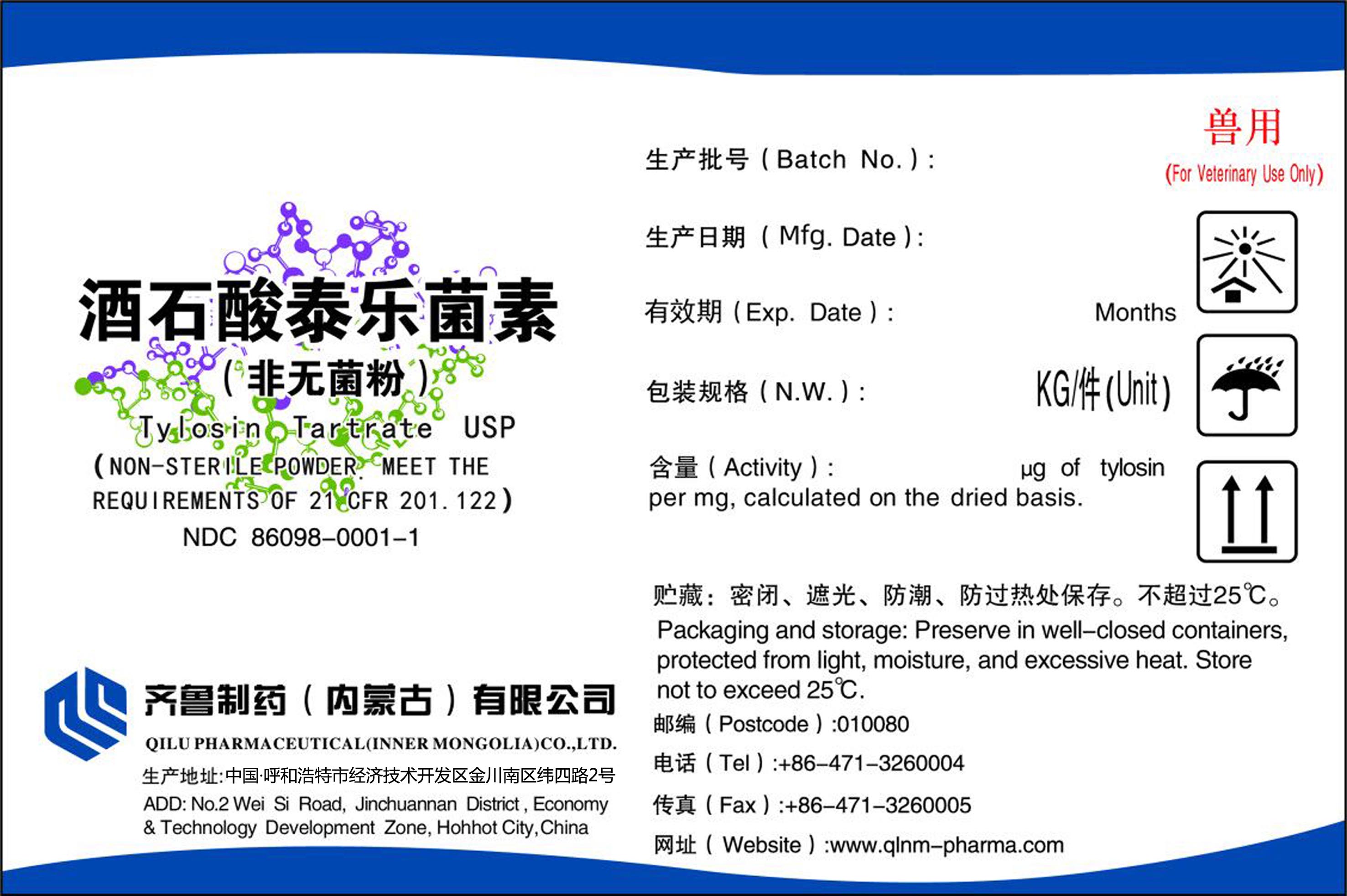 DRUG LABEL: Tylosin Tartrate
NDC: 86098-0001 | Form: powder
Manufacturer: Qilu Pharmaceutical (Inner Mongolia) Co.,Ltd.
Category: other | Type: BULK INGREDIENT - ANIMAL DRUG
Date: 20251223

ACTIVE INGREDIENTS: Tylosin Tartrate 15 kg/15 kg

PACKAGE LABEL

Tylosin Tartrate USP
(NON-STERILE POWDER.MEET THE
REQUIREMENTS OF 21 CFR 201.122)
NDC 86098-0001-1
QILU PHARMACEUTICAL (INNER MONGOLIA) CO.,LTD.
ADD:No.2 Wei Si Road, Jinchuannan District, Economy&Technology Development Zone, Hohhot City, China
Batch No.:
Mfg.Date:
Exp.Date: Months
N.W.: KG/Unit
Activity: μg of tylosin per mg,calculated on the dried basis.
Packaging and storage: Preserve in well-closed containers, protected from light, moisture, and excessive heat.Store not to exceed 25°C.
Postcode:010080
Tel:+86-471-3260004
Fax:+86-471-3260005
Website: www.qlnm-pharma.com